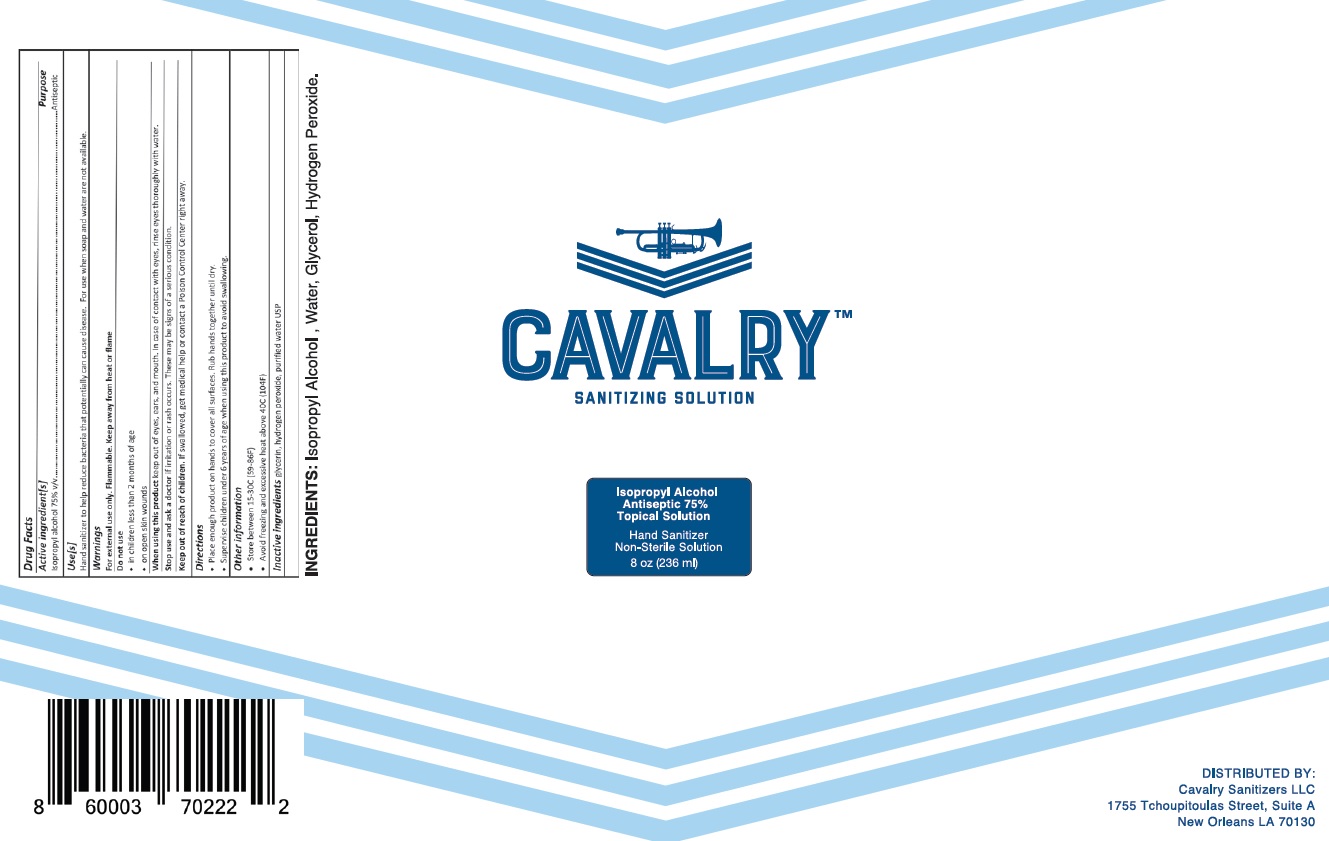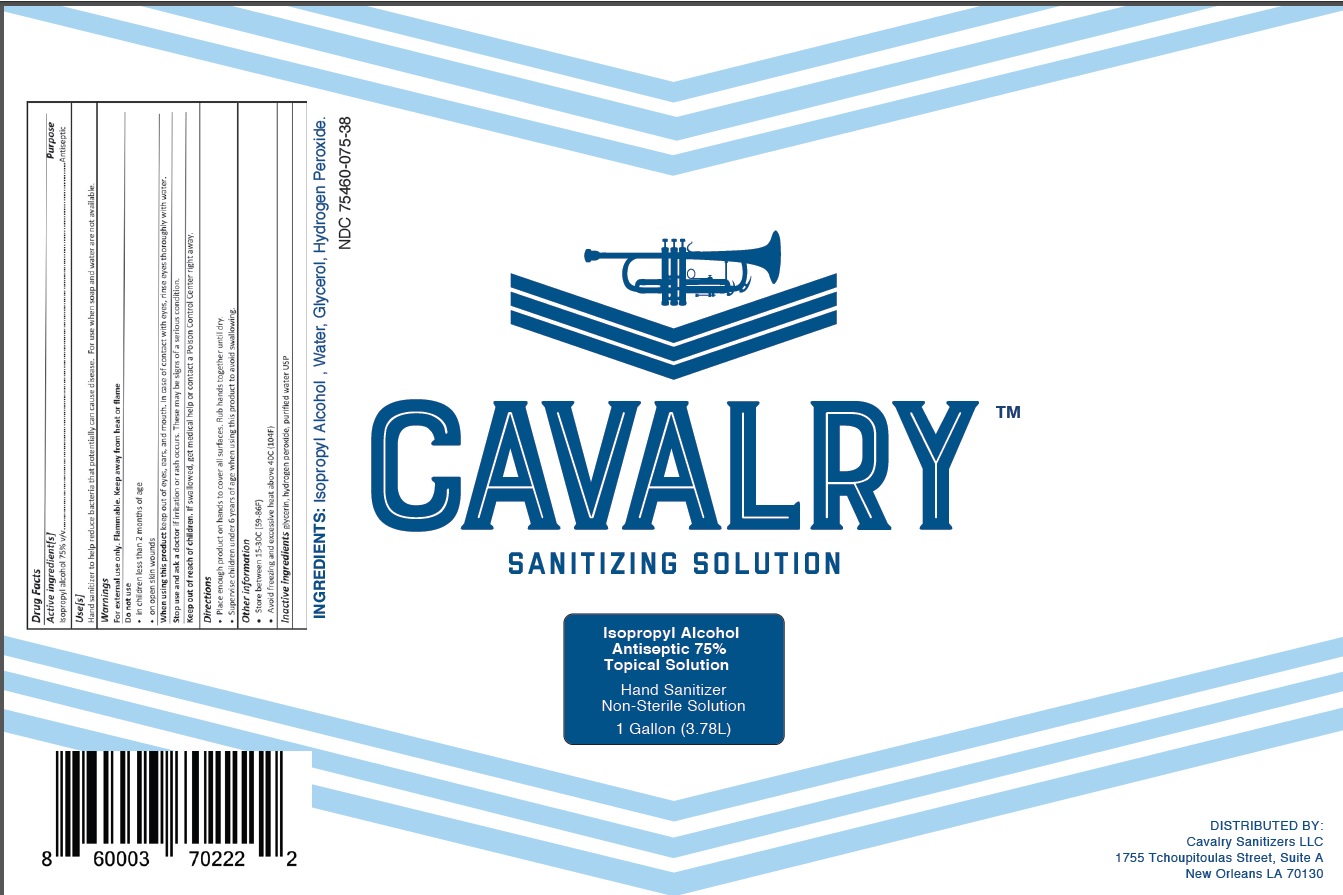 DRUG LABEL: CAVALRY
NDC: 75460-075 | Form: SOLUTION
Manufacturer: CAVALRY SANITIZERS, L.L.C.
Category: otc | Type: HUMAN OTC DRUG LABEL
Date: 20200724

ACTIVE INGREDIENTS: ISOPROPYL ALCOHOL 75 L/100 L
INACTIVE INGREDIENTS: GLYCERIN; HYDROGEN PEROXIDE; WATER

Active Ingredient(s)

Isopropyl Alcohol 75% v/v.

Purpose

Antiseptic

Use

Hand Sanitizer to help reduce bacteria that potentially can cause disease. For use when soap and water are not available.

Warnings

For external use only. Flammable. Keep away from heat or flame

Do not use

- in children less than 2 months of age
- on open skin wounds

When using this product

Keep out of eyes, ears, and mouth. In case of contact with eyes, rinse eyes thoroughly with water.

Stop use and ask a doctor

if irritation or rash occurs. These may be signs of a serious condition.

Keep out of reach of children.

If swallowed, get medical help or contact a Poison Control Center right away.

Directions

- Place enough product on hands to cover all surfaces. Rub hands together until dry.
- Supervise children under 6 years of age when using this product to avoid swallowing.

Other information

- Store between 15-30C (59-86F)
- Avoid freezing and excessive heat above 40C (104F)

Inactive ingredients

glycerin, hydrogen peroxide, purified water USP

Principal Display Panel

NDC 75460-075-38, 75460-075-08

CAVALRY SANITIZING SOLUTION

Isopropyl Alcohol 75% Topical Solution

Hand Sanitizer

Non-Sterile Solution

1 Gallon (3.78 L)

0.238 Litre (238 mL)